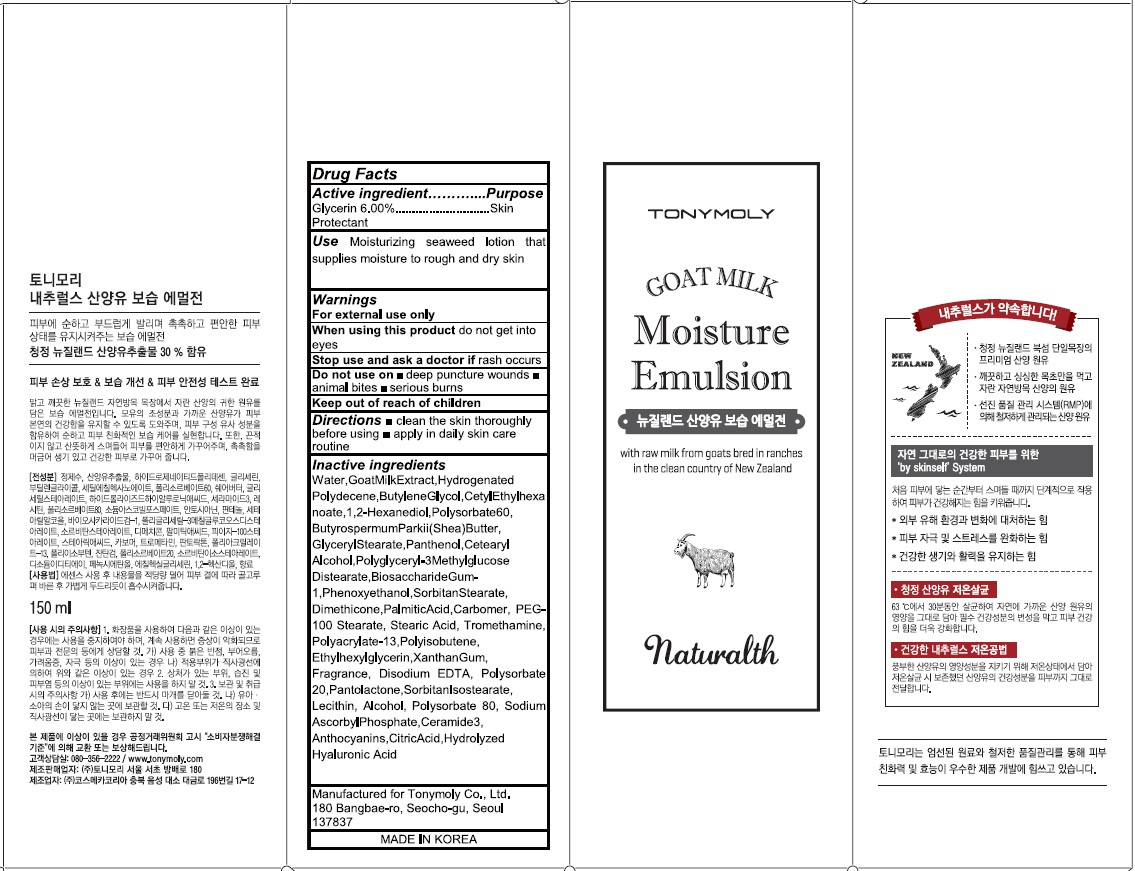 DRUG LABEL: NATURALTH GOAT MILK MOISTURE
NDC: 59078-280 | Form: EMULSION
Manufacturer: TONYMOLY CO.,LTD
Category: otc | Type: HUMAN OTC DRUG LABEL
Date: 20160526

ACTIVE INGREDIENTS: Glycerin 9 g/150 mL
INACTIVE INGREDIENTS: Water; Butylene Glycol

ACTIVE INGREDIENT

Active ingredient: Glycerin 6.00%

INACTIVE INGREDIENT

Inactive Ingredient: Water,Goat Milk Extract,Hydrogenated Polydecene,Butylene Glycol,CetylEthylhexanoate,1,2-Hexanediol,Polysorbate60, ButyrospermumParkii(Shea)Butter, GlycerylStearate,Panthenol,Cetearyl Alcohol,Polyglyceryl-3Methylglucose Distearate,BiosaccharideGum-1,Phenoxyethanol,SorbitanStearate, Dimethicone,PalmiticAcid,Carbomer, PEG-100 Stearate, Stearic Acid, Tromethamine, Polyacrylate-13,Polyisobutene, Ethylhexylglycerin,XanthanGum, Fragrance, Disodium EDTA, Polysorbate 20,Pantolactone,SorbitanIsostearate, Lecithin, Alcohol, Polysorbate 80, Sodium AscorbylPhosphate,Ceramide3, Anthocyanins,CitricAcid,Hydrolyzed Hyaluronic Acid

PURPOSE

Purpose: Skin Protectant

WARNINGS

Warnings: For external use only. When using this product do not get into eyes. Stop use and ask a doctor if rash occurs. Do not use on - deep puncture wounds - animal bites - serious burns Keep out of reach of children.

KEEP OUT OF REACH OF CHILDREN

Use

Use: Moisturizing seaweed lotion that supplies moisture to rough and dry skin

Directions

Directions: - clean the skin thoroughly before using - apply in daily skin care routine